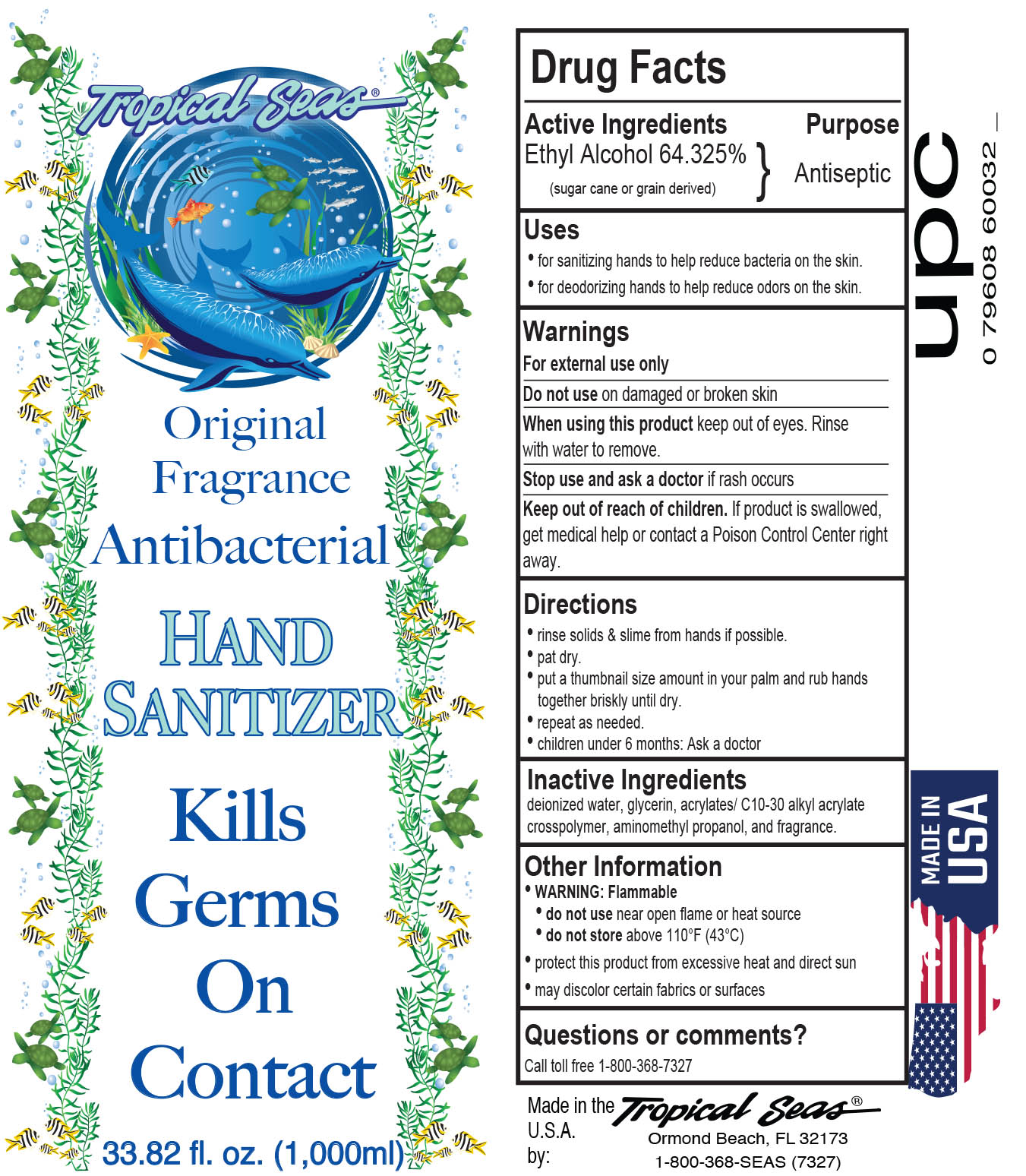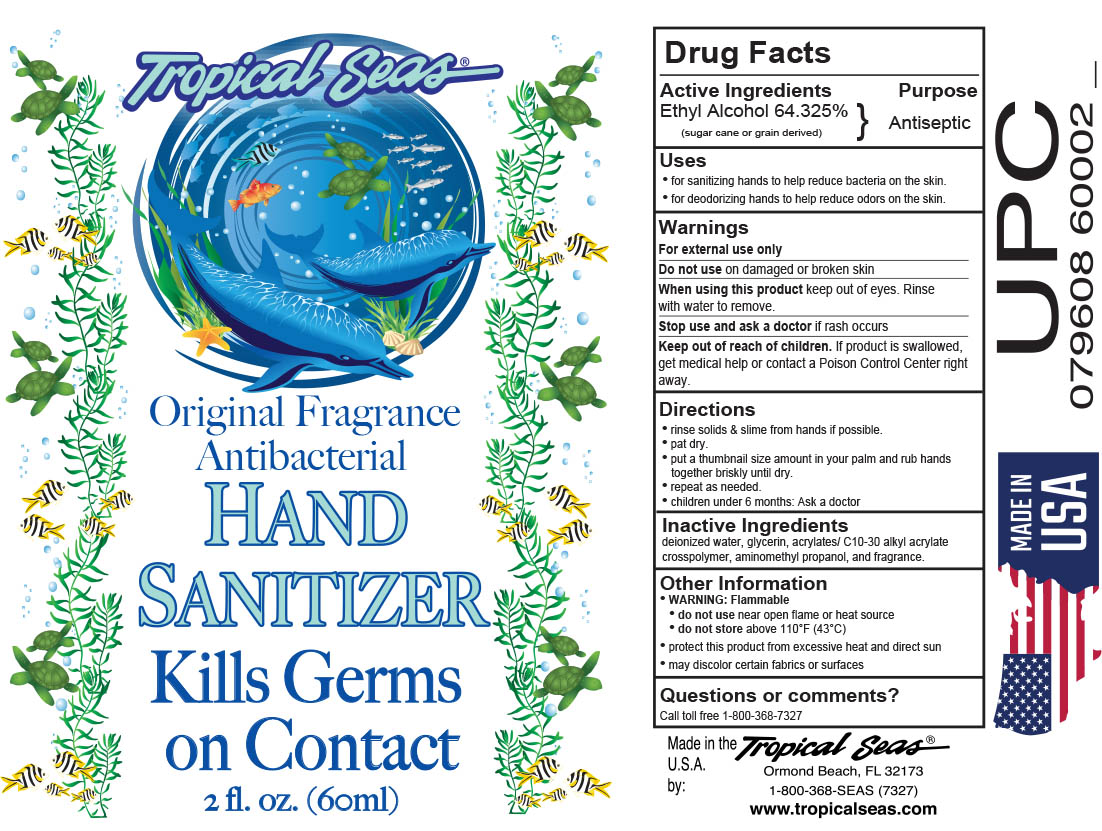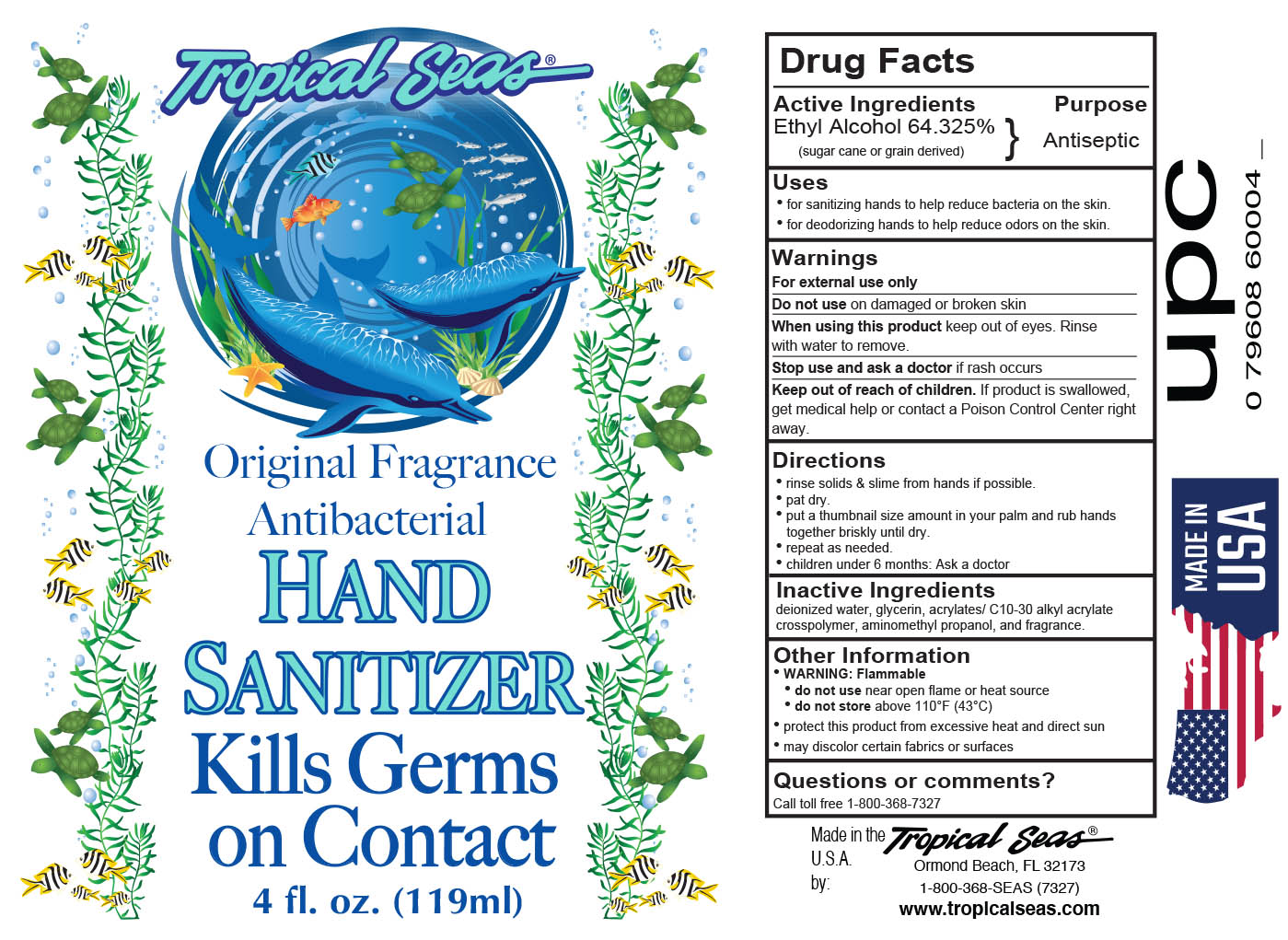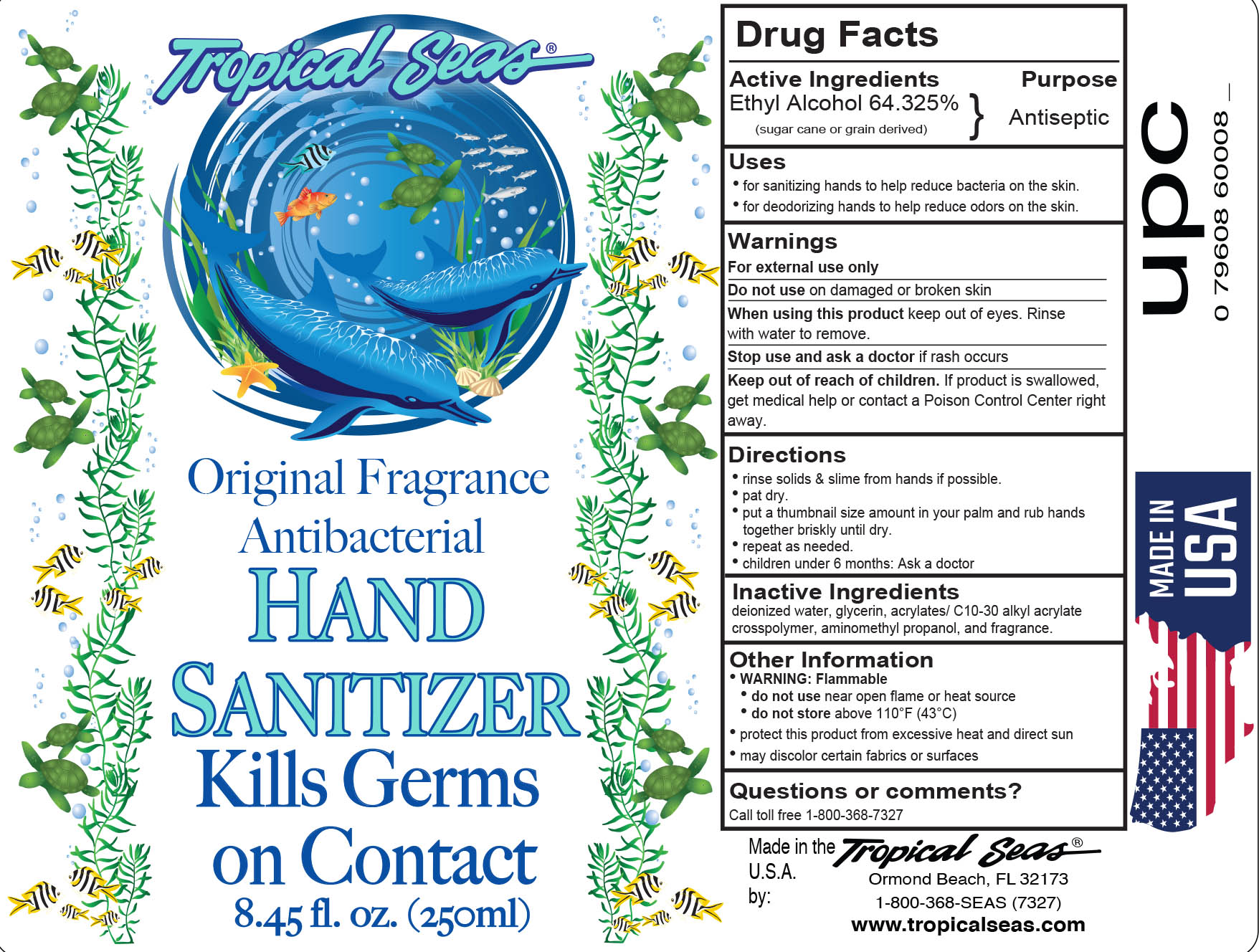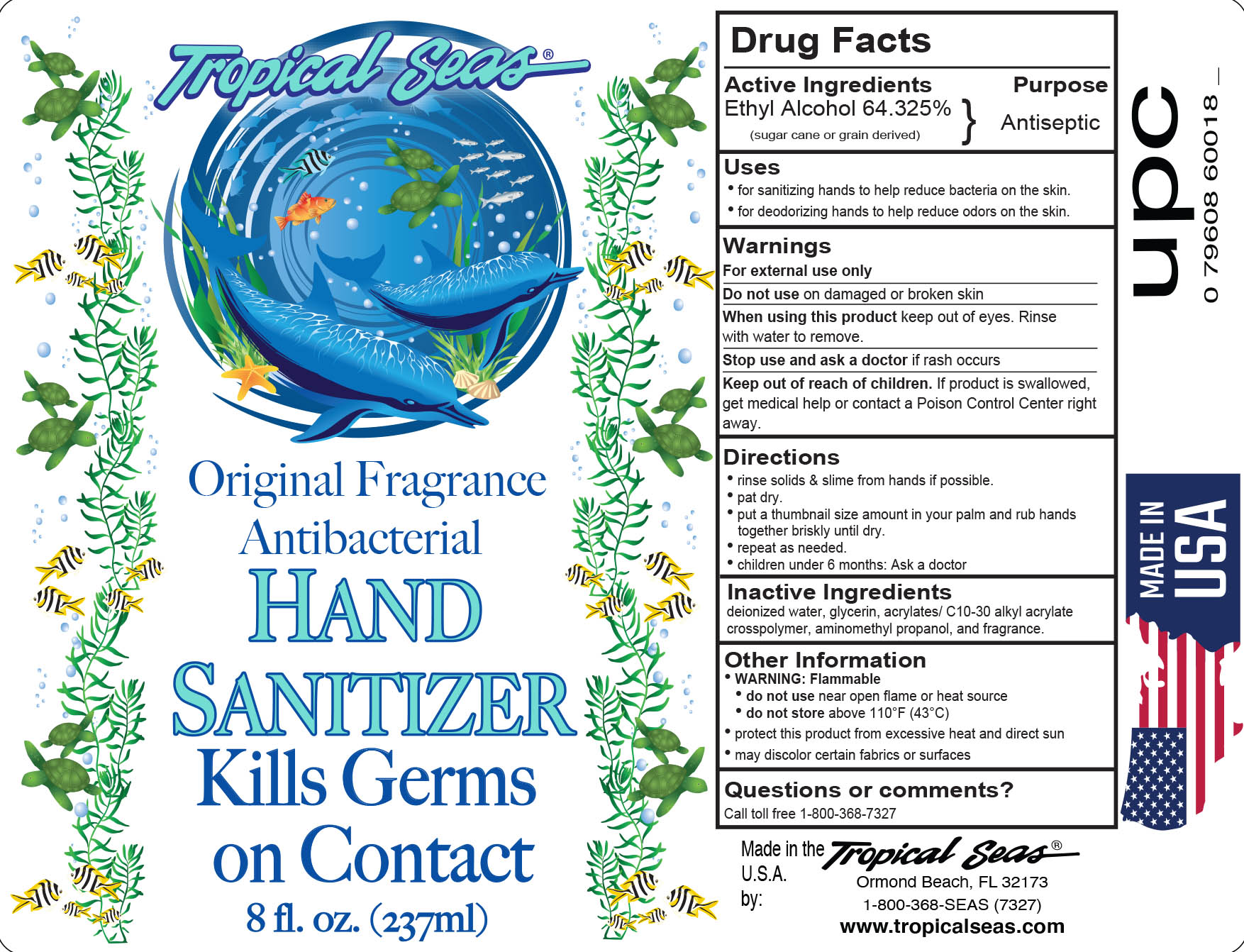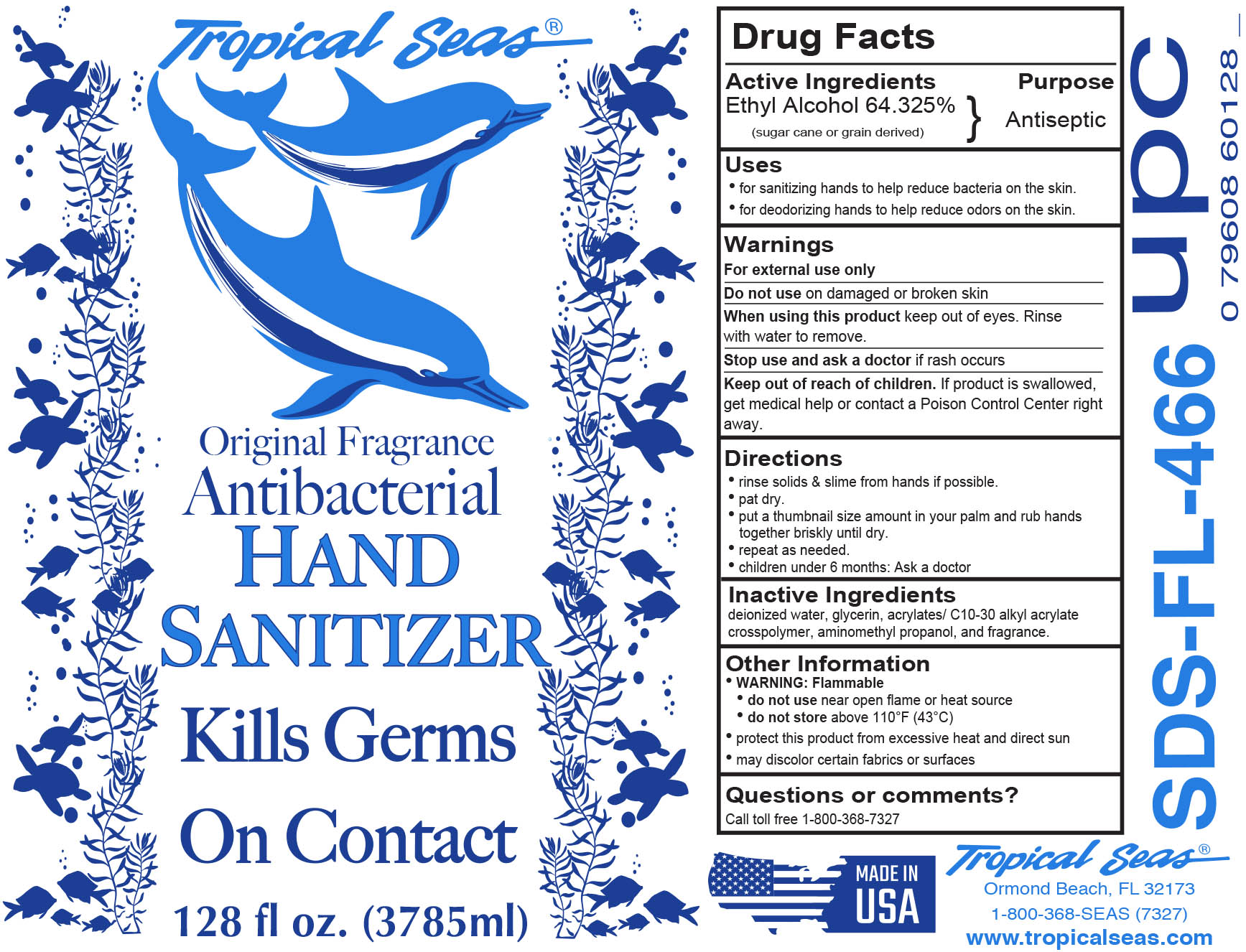 DRUG LABEL: Hand Sanitizer
NDC: 52854-600 | Form: LIQUID
Manufacturer: Tropical Seas, Inc.
Category: otc | Type: HUMAN OTC DRUG LABEL
Date: 20251104

ACTIVE INGREDIENTS: ALCOHOL 64.325 g/100 mL
INACTIVE INGREDIENTS: AMINOMETHYLPROPANOL; CARBOMER INTERPOLYMER TYPE A (ALLYL SUCROSE CROSSLINKED); WATER

Hand Sanitizer

Drug Facts

Active Ingredients

Ethyl Alcohol 64.325%

Purpose

Antiseptic

Uses

- for sanitizing hands to help reduce bacteria on the skin.
- for deodorizing hands to help reduce odors on the skin.

Warnings

For external use only

Do not use on damaged or broken skin

When using this product keep out of eyes. Rinse with water to remove.

Stop use and ask a doctor if rash occurs

Keep out of reach of children. If product is swallowed, get medical help or contact a Poison Control Center right away.

Directions

- rinse solids & slime from hands if possible.
- pat dry.
- put a thumbnail size amount in your palm and rub hands together briskly until dry.
- repeat as needed.
- children under 6 months: As a doctor

Inactive Ingredients

deionized water, glycerin, acrylates/c10-30 alkyl acrylate crosspolymer, aminomethyl propanol, and fragrance.

Other Information

Warning: Flammable

- do not use near open flame or heat source
- do not store above 110°F (43°C)
- protect this product from excessive heat and direct sun
- may discolor certain fabrics or surfaces

Questions or Comments?

Call toll free1-800-368-7327

Principal Display Panel - Bottle Label

60ml NDC: 52854-600-01

119ml NDC: 52854-600-02

237ml NDC: 52854-600-03

250ml NDC: 52854-600-04

1000ml NDC: 52854-600-05

3785ml NDC: 52854-600-06